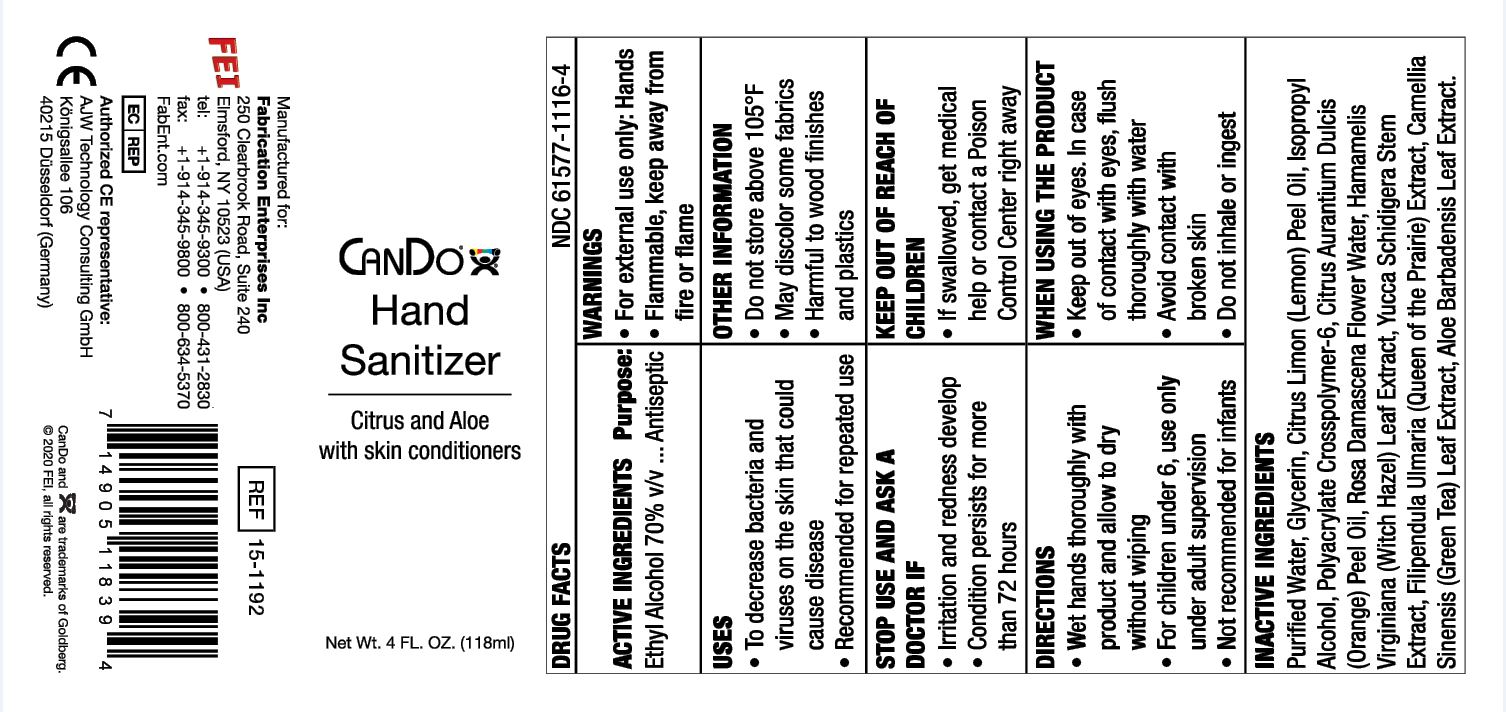 DRUG LABEL: CANDO HAND SANITIZER
NDC: 61577-1116 | Form: GEL
Manufacturer: SOMBRA COSMETICS
Category: otc | Type: HUMAN OTC DRUG LABEL
Date: 20200723

ACTIVE INGREDIENTS: ALCOHOL 70 mL/100 mL
INACTIVE INGREDIENTS: WATER; GLYCERIN; ISOPROPYL ALCOHOL; CAMELLIA SINENSIS FLOWER; ORANGE PEEL; AMMONIUM ACRYLOYLDIMETHYLTAURATE, DIMETHYLACRYLAMIDE, LAURYL METHACRYLATE AND LAURETH-4 METHACRYLATE COPOLYMER, TRIMETHYLOLPROPANE TRIACRYLATE CROSSLINKED (45000 MPA.S); ROSA DAMASCENA FLOWER; WITCH HAZEL; ALOE VERA LEAF; YUCCA SCHIDIGERA ROOT; FILIPENDULA RUBRA WHOLE; LEMON PEEL

CanDo Hand Sanitizer

Active Ingredients

Ethyl Alcohol 70%

Uses

To decrease bacteria and viruses on the skin that could cause disease. Recommended for repeated use.

Warnings

Flammable. Keep away from fire or flame. For external use only: hands.

Do not use

When using this product, do not use in or near the eyes. In case of contact, rinse eyes thoroughly with water.

When Using

Keep out of the eyes. In case of contact with eyes, flush thoroughly with water. Avoid contact with broken skin. Do not inhale or ingest

Stop use and ask a doctor if irritation and redness develop. Condition persists more than 72 hours.

Keep out of reach of children. If swallowed, get medical help or contact a Poison Control Center right away. For children under 6, use only under adult supervision. Not recommended for infants.

Directions

Wet hands thoroughly with product and allow to dry without wiping.

Other information

Do not store above 105F. May discolor some fabrics. Harmful to wood finishes and plastics.

Inactive ingredients

glycerin, purified water, isopropyl alcohol, polyacrylate crosspolymer-6, rosa damascena flower water, hamamelis virginiana (witch hazel) leaf extract, aloe barbadensis leaf juice, citrus aurantium dulcis (orange) peel oil, citrus limon (lemon) peel, oil, yucca schidigera stem extract, filipendula rubra extract, camellia sinensis (green tea) leaf extract.

Purpose

Antiseptic